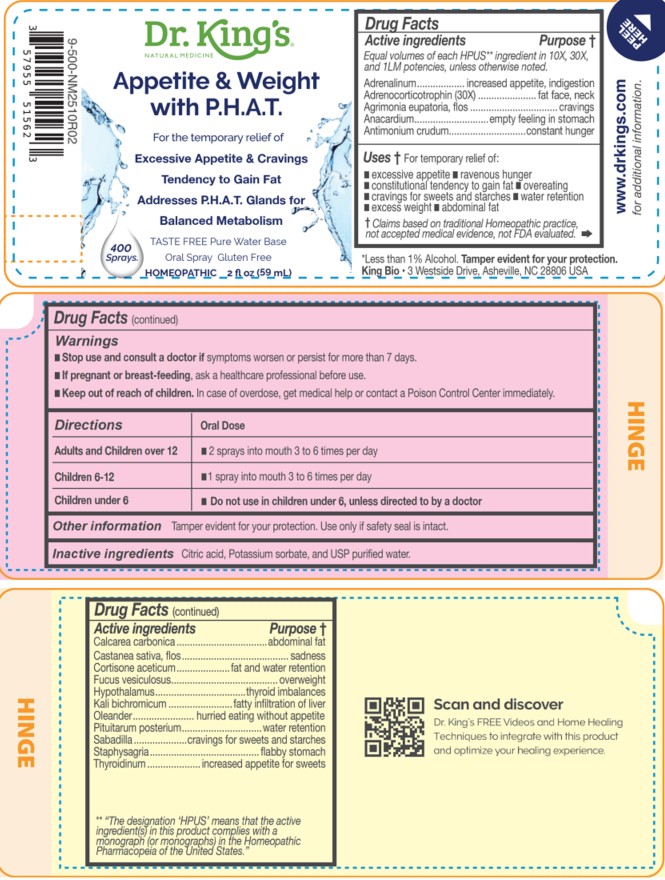 DRUG LABEL: Appetite and  Weight with P.H.A.T.
NDC: 57955-9989 | Form: LIQUID
Manufacturer: King Bio Inc.
Category: homeopathic | Type: HUMAN OTC DRUG LABEL
Date: 20260226

ACTIVE INGREDIENTS: EPINEPHRINE 10 [hp_X]/59 mL; CORTICOTROPIN 30 [hp_X]/59 mL; AGRIMONIA EUPATORIA FLOWER 10 [hp_X]/59 mL; SEMECARPUS ANACARDIUM JUICE 10 [hp_X]/59 mL; ANTIMONY TRISULFIDE 10 [hp_X]/59 mL; OYSTER SHELL CALCIUM CARBONATE, CRUDE 10 [hp_X]/59 mL; CASTANEA SATIVA FLOWER 10 [hp_X]/59 mL; CORTISONE ACETATE 10 [hp_X]/59 mL; FUCUS VESICULOSUS 10 [hp_X]/59 mL; BOS TAURUS HYPOTHALAMUS 10 [hp_X]/59 mL; POTASSIUM DICHROMATE 10 [hp_X]/59 mL; NERIUM OLEANDER LEAF 10 [hp_X]/59 mL; SUS SCROFA PITUITARY GLAND, POSTERIOR 10 [hp_X]/59 mL; SCHOENOCAULON OFFICINALE SEED 10 [hp_X]/59 mL; STAPHISAGRIA MACROSPERMA SEED 10 [hp_X]/59 mL; THYROID, UNSPECIFIED 10 [hp_X]/59 mL
INACTIVE INGREDIENTS: ANHYDROUS CITRIC ACID; POTASSIUM SORBATE; WATER

Appetite and Weight with P.H.A.T.

Active ingredients

Equal volumes of each HPUS** ingredient in 10X, 30X, and 1LM potencies, unless otherwise noted.

Adrenalinum, Adrenocorticotrophin (30X), Agrimonia eupatoria, flos, Anacardium, Antimonium crudum, Calcarea carbonica, Castanea sativa, flos, Cortisone aceticum, Fucus vesiculosus, Hypothalamus, Kali bichromicum, Oleander, Pituitarum posterium, Sabadilla, Staphysagria and Thyroidinum.

** "The designation 'HPUS’ means that the active ingredient(s) in this product complies with a monograph (or Monographs) in the Homeopathic Pharmacopeia of the United States.″

INDICATIONS AND USAGE

Uses † temporary relief of:

- excessive appetite
- ravenous hunger
- constitutional tendency to gain fat
- overeating
- cravings for sweets and starches
- water retention
- excess weight
- abdominal fat

† Claims based on traditional Homeopathic practice, not accepted medical evidence, not
FDA evaluated.

Questions

Appetite and Weight with P.H.A.T.

Dr. King's Natural Medicine

Taste free, Pure Water Base

Oral Spray Gluten Free

HOMEOPATHIC 2 fl oz (59 mL)

*Less than 1% Alcohol Tamper evident for your protection.

King Bio • 3 Westside Drive, Asheville, NC 28806 USA

www.DrKings.com
for additional information.

Dr. King's FREE Videos and Home
Healing Techniques to integrate with
this product and optimize your
healing experience.

Warnings

- Stop use and consult a doctor if symptoms worsen or persist for more than 7 days.
- If pregnant or breast-feeding, ask a healthcare professional before use.

- Keep out of reach of children. In case of overdose, get medical help or contact a Poison Control Center immediately.

DOSAGE AND ADMINISTRATION

Directions | Oral Dose
Adults and Children over 12 | - 2 sprays into mouth 3 to 6 times per day
Children 6-12 | - 1 spray into mouth 3 to 6 times per day
Children under 6 | - Do not use in children under 6, unless directed to by a doctor

Other information

Tamper evident for your protection. Use only if safety seal is intact.

Inactive Ingredients

Citric Acid, Potassium Sorbate, and USP purified Water.

PURPOSE

Equal volumes of each HPUS ingredient in 10X, 30X, and 1LM
potencies, unless otherwise noted.

Active ingredients Purpose †

**“HPUS” indicates the active ingredients are in the official Homeopathic
Pharmacopeia of the United States.

Adrenalinum..............................................increased appetite, indigestion
Adrenocorticotrophin (30X) ................................................fat face, neck
Agrimonia eupatoria, flos............................................................cravings
Anacardium orientale .........................................empty feeling in stomach
Antimonium crudum .......................................................constant hunger
Calcarea carbonica .............................................................abdominal fat

Castanea sativa, flos...................................................................sadness
Cortisone aceticum ................................................fat and water retention
Fucus vesiculosus....................................................................overweight
Hypothalamus..............................................................thyroid imbalances
Kali bichromicum....................................................fatty infiltration of liver
Oleander....................................................hurried eating without appetite
Pituitarum posterium ........................................................water retention
Sabadilla..................................................cravings for sweets and starches
Staphysagria.....................................................................flabby stomach
Thyroidinum .................................................increased appetite for sweets

** "The designation 'HPUS’ means that the active ingredient(s) in this product complies with a monograph (or Monographs) in the Homeopathic Pharmacopeia of the United States.″

† Claims based on traditional Homeopathic practice, not accepted medical evidence, not
FDA evaluated.